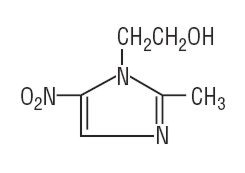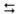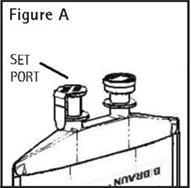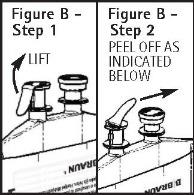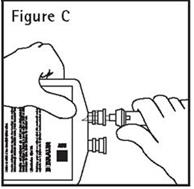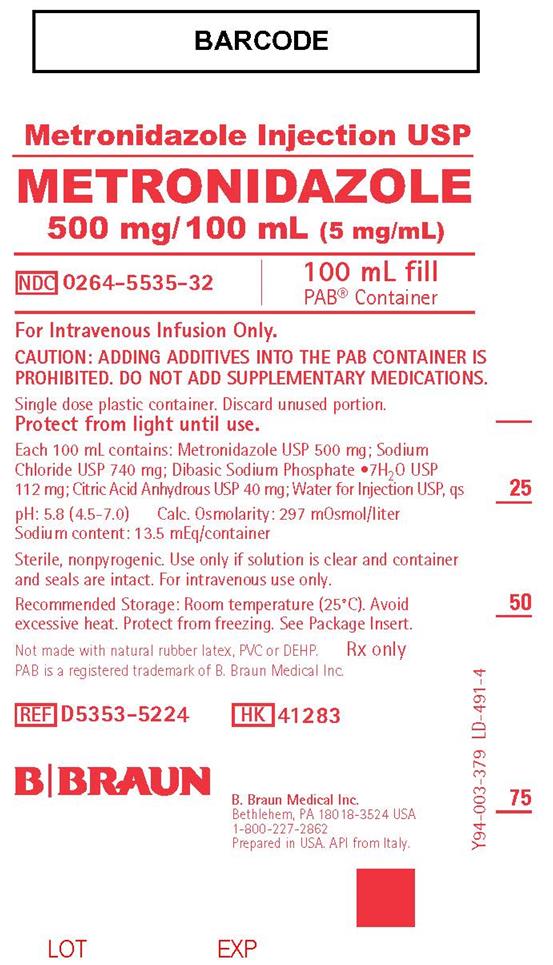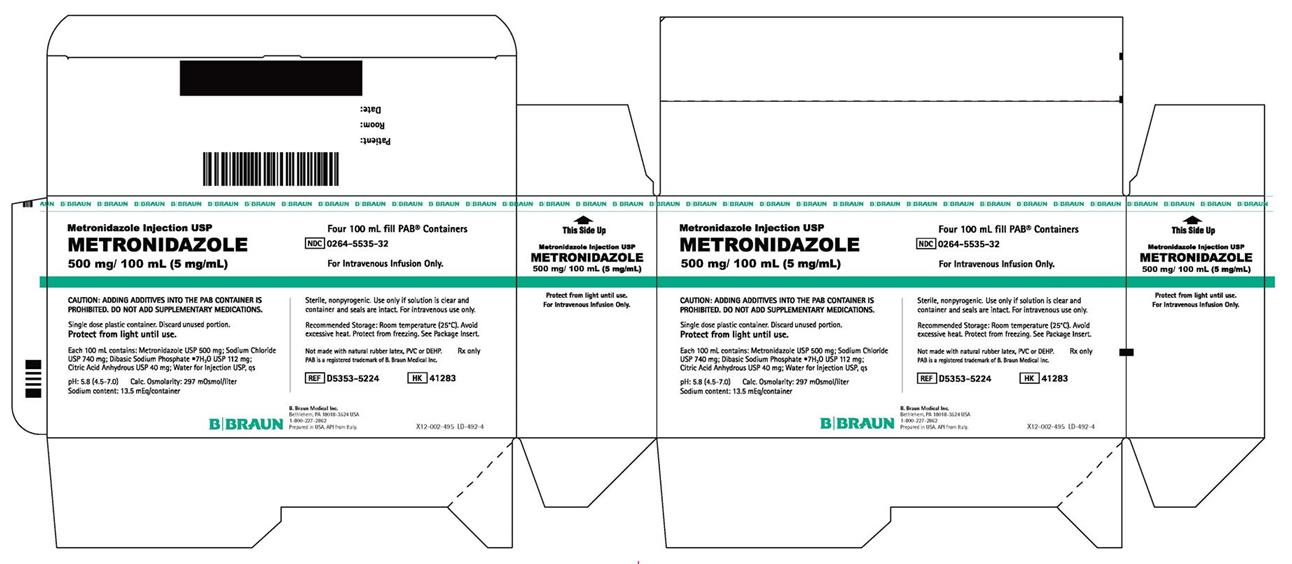 DRUG LABEL: METRONIDAZOLE
NDC: 0264-5535 | Form: SOLUTION
Manufacturer: B. Braun Medical Inc.
Category: prescription | Type: HUMAN PRESCRIPTION DRUG LABEL
Date: 20250325

ACTIVE INGREDIENTS: METRONIDAZOLE 500 mg/100 mL
INACTIVE INGREDIENTS: SODIUM CHLORIDE 740 mg/100 mL; SODIUM PHOSPHATE, DIBASIC 112 mg/100 mL; ANHYDROUS CITRIC ACID 40 mg/100 mL; WATER

Metronidazole Injection USP
METRONIDAZOLE

500 mg/ 100 mL (5 mg/mL)

Sterile

Rx only

For Intravenous Infusion Only.

To reduce the development of drug-resistant bacteria and maintain the effectiveness of Metronidazole Injection USP and other antibacterial drugs, Metronidazole Injection USP should be used only to treat or prevent infections that are proven or strongly suspected to be caused by bacteria.

WARNING

Metronidazole has been shown to be carcinogenic in mice and rats (see PRECAUTIONS). Its use, therefore, should be reserved for the conditions described in the INDICATIONS AND USAGE section below.

DESCRIPTION

Metronidazole Injection USP is a sterile, parenteral dosage form of metronidazole in water.

Each 100 mL of Metronidazole Injection USP contains a sterile, nonpyrogenic, isotonic, buffered solution of Metronidazole USP 500 mg, Sodium Chloride USP 740 mg, Dibasic Sodium Phosphate•7H2O USP 112 mg, and Citric Acid Anhydrous USP 40 mg in Water for Injection USP. Metronidazole Injection USP has a calculated osmolarity of 297 mOsmol/liter and a pH of 5.8 (4.5–7.0). Sodium content: 13.5 mEq/container.

Metronidazole is classified as a nitroimidazole antimicrobial and is administered by the intravenous route.

Metronidazole USP is chemically designated 2-methyl-5-nitroimidazole-1-ethanol (C6H9N3O3):

Not made with natural rubber latex, PVC, or DEHP.

The plastic container is a copolymer of ethylene and propylene formulated and developed for parenteral drugs. The copolymer contains no plasticizers. The safety of the plastic container has been confirmed by biological evaluation procedures.

The material passes Class VI testing as specified in the U.S. Pharmacopeia for Biological Tests – Plastic Containers. The container/solution unit is a closed system and is not dependent upon entry of external air during administration. No vapor barrier is necessary.

CLINICAL PHARMACOLOGY

Metronidazole is a synthetic antibacterial compound. Disposition of metronidazole in the body is similar for both oral and intravenous dosage forms, with an average elimination half-life in healthy humans of eight hours.

The major route of elimination of metronidazole and its metabolites is via the urine (60 to 80% of the dose), with fecal excretion accounting for 6 to 15% of the dose. The metabolites that appear in the urine result primarily from side-chain oxidation (1-[β-hydroxyethyl]-2-hydroxymethyl-5-nitroimidazole and 2-methyl-5-nitroimidazole-1-yl-acetic acid) and glucuronide conjugation, with unchanged metronidazole accounting for approximately 20% of the total. Renal clearance of metronidazole is approximately 10 mL/min/1.73 m^2.

Metronidazole is the major component appearing in the plasma, with lesser quantities of the 2-hydroxymethyl metabolite also being present. Less than 20% of the circulating metronidazole is bound to plasma proteins. Both the parent compound and the metabolite possess in vitro bactericidal activity against most strains of anaerobic bacteria.

Metronidazole appears in cerebrospinal fluid, saliva, and human milk in concentrations similar to those found in plasma. Bactericidal concentrations of metronidazole have also been detected in pus from hepatic abscesses.

Plasma concentrations of metronidazole are proportional to the administered dose. An eight-hour intravenous infusion of 100 to 4,000 mg of metronidazole in normal subjects showed a linear relationship between dose and peak plasma concentration.

In patients treated with metronidazole injection using a dosage regimen of 15 mg/kg loading dose followed six hours later by 7.5 mg/kg every six hours, peak steady-state plasma concentrations of metronidazole averaged 25 mcg/mL with trough (minimum) concentrations averaging 18 mcg/mL.

Decreased renal function does not alter the single-dose pharmacokinetics of metronidazole. However, plasma clearance of metronidazole is decreased in patients with decreased liver function.

Pediatric Patients

In one study newborn infants appeared to demonstrate diminished capacity to eliminate metronidazole. The elimination half-life, measured during the first three days of life, was inversely related to gestational age. In infants whose gestational ages were between 28 and 40 weeks, the corresponding elimination half-lives ranged from 109 to 22.5 hours.

Two other trials included infants 23-48 weeks post-menstrual age, (0-80 days postnatal age) with complicated intra-abdominal infections. Clearance increased with increasing post-menstrual age, while volume of distribution and half-life decreased (see PRECAUTIONS, Pediatric Use and DOSAGE AND AMINISTRATION).

MICROBIOLOGY:

Mechanism of Action

Metronidazole, a nitroimidazole, exerts antibacterial effects in an anaerobic environment against most obligate anaerobes. Once metronidazole enters the organism by passive diffusion and activated in the cytoplasm of susceptible anaerobic bacteria, it is reduced; this process includes intra-cellular electron transport donors such as ferredoxin and transfer of an electron to the nitro group of the metronidazole leading to formation of a short-lived nitroso free radical. Because of this alteration of the metronidazole molecule, a concentration gradient is created and maintained which promotes the drug’s intracellular transport. The reduced form of metronidazole and free radicals may interact with DNA leading to inhibition of DNA synthesis, DNA degradation, and death of bacteria. The precise mechanism of action of metronidazole is unclear.

Drug Resistance

A potential for development of resistance exists against metronidazole.

Resistance may be due to multiple mechanisms that include decreased uptake of the drug, altered reduction efficiency, overexpression of the efflux pumps, inactivation of the drug, and/or increased DNA damage repair.

Metronidazole does not possess any clinically relevant activity against facultative anaerobes or obligate aerobes.

Antimicrobial Activity

Metronidazole has been shown to be active against most isolates of the following bacteria both in vitro and clinical infections as described in the INDICATIONS AND USAGE section.

Gram negative anaerobes:

Bacteroides fragilis group (B. fragilis, B. distasonis, B. ovatus, B. thetaiotaomicron, B. vulgatus)

Fusobacterium species

Gram positive anaerobes:

Clostridium species

Eubacterium species

Peptococcus species

Peptostreptococcus species

The following in vitro data are available, but their clinical significance is unknown: Metronidazole exhibits in vitro minimal inhibitory concentrations (MIC’s) of 8 mcg/mL or less against most (≥90%) isolates of the following bacteria; however, the safety and effectiveness of metronidazole in treating clinical infections due to these bacteria have not been established in adequate and well-controlled clinical trials.

Gram negative anaerobes

Bacteroides fragilis group (B. caccae, B. uniformis)

Prevotella species (P. bivia, P. buccae, P. disiens)

Susceptibility Testing:

For specific information regarding susceptibility test interpretive criteria, and associated test methods and quality control standards recognized by FDA for this drug, please see: http://www.fda.gov/STIC.

INDICATIONS AND USAGE

To reduce the development of drug-resistant bacteria and maintain the effectiveness of Metronidazole Injection USP and other antibacterial drugs, Metronidazole Injection USP should be used only to treat or prevent infections that are proven or strongly suspected to be caused by susceptible bacteria. When culture and susceptibility information are available, they should be considered in selecting or modifying antibacterial therapy. In the absence of such data, local epidemiology and susceptibility patterns may contribute to the empiric selection of therapy.

TREATMENT OF ANAEROBIC INFECTIONS

Metronidazole Injection is indicated in the treatment of serious infections caused by susceptible anaerobic bacteria. Indicated surgical procedures should be performed in conjunction with Metronidazole Injection therapy. In a mixed aerobic and anaerobic infection, antibacterial drugs appropriate for the treatment of the aerobic infection should be used in addition to Metronidazole Injection.

Metronidazole Injection USP is effective in Bacteroides fragilis infections resistant to clindamycin, chloramphenicol, and penicillin.

- Intra-Abdominal Infections, including peritonitis, intra-abdominal abscess, and liver abscess, caused by Bacteroides species including the B. fragilis group (B. fragilis, B. distasonis, B. ovatus, B. thetaiotaomicron, B. vulgatus), Clostridium species, Eubacterium species, Peptococcus species, and Peptostreptococcus species in adults and pediatric patients less than 4 months of age.
- Skin and Skin Structure Infections caused by Bacteroides species including the B. fragilis group, Clostridium species, Peptococcus species, Peptostreptococcus species, and Fusobacterium species in adults.
- Gynecologic Infections, including endometritis, endomyometritis, tubo-ovarian abscess, and post-surgical vaginal cuff infection, caused by Bacteroides species including the B. fragilis group, Clostridium species, Peptococcus species, and Peptostreptococcus species in adults.
- Bacterial Septicemia caused by Bacteroides species including the B. fragilis group and Clostridium species in adults.
- Bone and Joint Infections, as adjunctive therapy, caused by Bacteroides species including the B. fragilis group in adults.
- Central Nervous System (CNS) Infections, including meningitis and brain abscess, caused by Bacteroides species including the B. fragilis group in adults.
- Lower Respiratory Tract Infections, including pneumonia, empyema, and lung abscess, caused by Bacteroides species including the B. fragilis group in adults.
- Endocarditis caused by Bacteroides species including the B. fragilis group in adults.

PROPHYLAXIS INDICATION

The prophylactic administration of Metronidazole Injection preoperatively, intraoperatively, and postoperatively may reduce the incidence of postoperative infection in adult patients undergoing elective colorectal surgery which is classified as contaminated or potentially contaminated.

Prophylactic use of Metronidazole Injection should be discontinued within 12 hours after surgery. If there are signs of infection, specimens for cultures should be obtained for the identification of the causative organism(s) so that appropriate therapy may be given (see DOSAGE AND ADMINISTRATION).

Usage

To reduce the development of drug-resistant bacteria and maintain the effectiveness of metronidazole and other antibacterial drugs, metronidazole should be used only to treat or prevent infections that are proven or strongly suspected to be caused by susceptible bacteria. When culture and susceptibility information are available, they should be considered in selecting or modifying antimicrobial therapy. In the absence of such data, local epidemiology and susceptibility patterns may contribute to the empiric selection of therapy.

CONTRAINDICATIONS

- Hypersensitivity

Metronidazole Injection is contraindicated in patients with a prior history of hypersensitivity to metronidazole or other nitroimidazole derivatives.

- Psychotic Reaction with Disulfiram
  Use of oral metronidazole is associated with psychotic reactions in alcoholic patients who were using disulfiram concurrently. Do not administer metronidazole to patients who have taken disulfiram within the last two weeks (see PRECAUTIONS-Drug Interactions).
- Interaction with Alcohol
  Use of oral metronidazole is associated with a disulfiram-like reaction to alcohol, including abdominal cramps, nausea, vomiting, headaches, and flushing. Discontinue consumption of alcohol or products containing propylene glycol during and for at least three days after therapy with metronidazole (see PRECAUTIONS-Drug Interactions).
- Cockayne Syndrome

Metronidazole Injection is contraindicated in patients with Cockayne syndrome. Severe irreversible hepatotoxicity/acute liver failure with fatal outcomes have been reported after initiation of metronidazole in patients with Cockayne syndrome (see ADVERSE REACTIONS).

WARNINGS

Severe cutaneous adverse reactions (SCARs) including toxic epidermal necrolysis (TEN), Stevens-Johnson syndrome (SJS), drug reaction with eosinophilia and systemic symptoms (DRESS), and acute generalized exanthematous pustulosis (AGEP) have been reported with the use of metronidazole. Symptoms can be serious and potentially life threatening. If symptoms or signs of SCARs develop, discontinue Metronidazole injection immediately and institute appropriate therapy.

CENTRAL AND PERIPHERAL NERVOUS SYSTEM EFFECTS:

Convulsive seizures, encephalopathy, aseptic meningitis, optic and peripheral neuropathy, the latter characterized mainly by numbness or paresthesia of an extremity, have been reported in patients treated with metronidazole products. Since persistent peripheral neuropathy has been reported in some patients receiving prolonged oral administration of metronidazole, patients should be observed carefully. The appearance of abnormal neurologic signs demands the prompt evaluation of the benefit/risk ratio of the continuation of therapy.

PRECAUTIONS

GENERAL:

Patients with severe hepatic disease metabolize metronidazole slowly, with resultant accumulation of metronidazole and its metabolites in the plasma. Accordingly, for such patients, doses below those usually recommended should be administered cautiously.

Administration of solutions containing sodium ions may result in sodium retention. Care should be taken when administering Metronidazole Injection to patients receiving corticosteroids or to patients predisposed to edema.

Known or previously unrecognized candidiasis may present more prominent symptoms during therapy with Metronidazole Injection and requires treatment with a candicidal agent.

Prescribing Metronidazole Injection in the absence of a proven or strongly suspected bacterial infection or a prophylactic indication is unlikely to provide benefit to the patient and increases the risk of the development of drug-resistant bacteria.

INFORMATION FOR PATIENTS:

Patients should be counseled that antibacterial drugs including Metronidazole Injection USP should only be used to treat bacterial infections. They do not treat viral infections (e.g., the common cold). When Metronidazole Injection USP is prescribed to treat a bacterial infection, patients should be told that although it is common to feel better early in the course of therapy, the medication should be taken exactly as directed. Skipping doses or not completing the full course of therapy may (1) decrease the effectiveness of the immediate treatment and (2) increase the likelihood that bacteria will develop resistance and will not be treatable by Metronidazole Injection USP or other antibacterial drugs in the future.

Advise patients that Metronidazole Injection may increase the risk of serious and sometimes fatal dermatologic reactions, including toxic epidermal necrolysis (TEN), Stevens-Johnson syndrome (SJS), and drug reaction with eosinophilia and systemic symptoms (DRESS). Instruct the patient to be alert for skin rash, blisters, fever or other signs and symptoms of these hypersensitivity reactions. Advise patients to stop Metronidazole injection immediately if they develop any type of rash and seek medical attention.

LABORATORY TESTS:

Metronidazole is a nitroimidazole, and Metronidazole Injection USP should be used with caution in patients with evidence of or history of blood dyscrasia. A mild leukopenia has been observed during its administration; however, no persistent hematologic abnormalities attributable to metronidazole have been observed in clinical studies. Total and differential leukocyte counts are recommended before and after therapy.

DRUG INTERACTIONS:

Metronidazole has been reported to potentiate the anticoagulant effect of warfarin and other oral coumarin anticoagulants, resulting in a prolongation of prothrombin time. This possible drug interaction should be considered when Metronidazole Injection USP is prescribed for patients on this type of anticoagulant therapy.

The simultaneous administration of drugs that induce microsomal liver enzymes, such as phenytoin or phenobarbital, may accelerate the elimination of metronidazole, resulting in reduced plasma levels; impaired clearance of phenytoin has also been reported.

The simultaneous administration of drugs that decrease microsomal liver enzyme activity, such as cimetidine, may prolong the half-life and decrease plasma clearance of metronidazole.

Alcoholic beverages should not be consumed during metronidazole therapy because abdominal cramps, nausea, vomiting, headaches, and flushing may occur.

Psychotic reactions have been reported in alcoholic patients who are using metronidazole and disulfiram concurrently. Metronidazole should not be given to patients who have taken disulfiram within the last two weeks.

QT prolongation has been reported, particularly when metronidazole was administered with drugs with the potential for prolonging the QT interval.

DRUG/LABORATORY TEST INTERACTIONS:

Metronidazole may interfere with certain types of determinations of serum chemistry values, such as aspartate aminotransferase (AST, SGOT), alanine aminotransferase (ALT, SGPT), lactate dehydrogenase (LDH), triglycerides, and hexokinase glucose. Values of zero may be observed. All of the assays in which interference has been reported involve enzymatic coupling of the assay to oxidation-reduction of nicotinamide adenine dinucleotide (NAD^+ NADH). Interference is due to the similarity in absorbance peaks of NADH (340 nm) and metronidazole (322 nm) at pH 7.

CARCINOGENESIS, MUTAGENESIS, IMPAIRMENT OF FERTILITY

Tumorigenicity in Rodents:

Metronidazole has shown evidence of carcinogenic activity in studies involving chronic, oral administration in mice and rats, but similar studies in the hamster gave negative results. Also, metronidazole has shown mutagenic activity in a number of in vitro assay systems, but studies in mammals (in vivo) failed to demonstrate a potential for genetic damage.

PREGNANCY:

TERATOGENIC EFFECTS

Teratogenic Effects. Metronidazole crosses the placental barrier and enters the fetal circulation rapidly. Reproduction studies have been performed in rats at doses up to five times the human dose and have revealed no evidence of impaired fertility or harm to the fetus due to metronidazole. Metronidazole administered intraperitoneally to pregnant mice at approximately the human dose caused fetotoxicity; administered orally to pregnant mice, no fetotoxicity was observed. There are, however, no adequate and well-controlled studies in pregnant women. Because animal reproduction studies are not always predictive of human response, and because metronidazole is a carcinogen in rodents, this drug should be used during pregnancy only if clearly needed (see CONTRAINDICATIONS).

NURSING MOTHERS:

Metronidazole is secreted in human milk in concentrations similar to those found in plasma. Because of the potential for tumorigenicity shown for metronidazole in mouse and rat studies, a decision should be made whether to discontinue nursing or to discontinue the drug, taking into account the importance of the drug to the mother.

PEDIATRIC USE:

Pediatric Patients Less than 4 Months of Age

The safety and effectiveness of Metronidazole Injection have been established for the treatment of intra-abdominal infections in pediatric patients from birth to less than 4 months. Use of Metronidazole Injection in this age group is supported by evidence from data in adults with additional pharmacokinetic and safety data in pediatric patients from birth to less than 4 months of age.

A partially randomized, open-label, phase 2/3 study of intravenous Metronidazole Injection in combination with other intravenous antibacterial drugs was conducted in 62 preterm infants (≤ 33 weeks gestational age at birth, and postnatal age <121 days) and 55 late preterm and term infants (≥ 34 weeks gestational age at birth, and postnatal age <121 days), with complicated intra-abdominal infections. The primary objective of this study was to evaluate the safety of metronidazole-containing regimens, which were administered for up to 10 days. The adverse reactions reported in patients receiving metronidazole-containing regimens were comparable to patients receiving other antibacterial regimens in the study and generally similar to adverse reactions described in adults.

The safety and effectiveness of Metronidazole Injection in pediatric patients less than 4 months of age have not been established for (1) the treatment of anaerobic infections other than intra-abdominal infections or for (2) prophylaxis of postoperative infections (see INDICATIONS AND USAGE, CLINICAL PHARMACOLOGY, Pediatric Patients and DOSAGE AND ADMINISTRATION).

Pediatric Patients 4 Months of Age and Older

The safety and effectiveness of Metronidazole Injection in pediatric patients 4 months of age and older have not been established.

ADVERSE REACTIONS

The following are the most serious adverse reactions reported in patients treated with metronidazole and are also described elsewhere in the labeling: convulsive seizures, encephalopathy, aseptic meningitis, optic and peripheral neuropathy (characterized mainly by numbness or paresthesia of an extremity) (see WARNINGS).

The following adverse reactions associated with the use of metronidazole products were identified in clinical studies or postmarketing reports or published literature. Because some of these reactions were reported voluntarily from a population of uncertain size, it is not always possible to reliably estimate their frequency or establish a causal relationship to drug exposure.

GASTROINTESTINAL: Nausea, anorexia, vomiting, abdominal discomfort, diarrhea, an unpleasant metallic taste, epigastric distress, abdominal cramping, constipation and pancreatitis.

MOUTH: A sharp metallic taste. Furry tongue, glossitis, and stomatitis have occurred; these may be associated with a sudden overgrowth of Candida which may occur during therapy with metronidazole.

HEMATOPOIETIC: Reversible neutropenia (leukopenia); thrombocytopenia, eosinophilia.

HEPATOBILIARY DISORDERS: Hepatotoxicity and liver failure especially in patients with Cockayne syndrome (see CONTRAINDICATIONS), jaundice.

CARDIOVASCULAR: QT prolongation has been reported, particularly when metronidazole was administered with drugs with the potential for prolonging the QT interval. Flattening of the T-wave may be seen in electrocardiographic tracings.

SKIN AND SUBCUTANEOUS DISORDERS: Toxic epidermal necrolysis, Stevens-Johnson syndrome, Drug Reaction with Eosinophilia and Systemic Symptoms (DRESS), erythematous rash, bullae, pruritus, swelling face, urticaria, and hyperhidrosis.

CENTRAL NERVOUS SYSTEM: Encephalopathy, aseptic meningitis, convulsive seizures, optic neuropathy, peripheral neuropathy (mainly numbness or paresthesia of an extremity), dizziness, vertigo, incoordination, ataxia, confusion, psychosis, dysarthria, irritability, depression, weakness, headache, tinnitus, hearing impairment, hearing loss, and insomnia.

LABORATORY INVESTIGATIONS: Hepatic enzymes increased.

HYPERSENSITIVITY: Toxic epidermal necrolysis (TEN), Stevens-Johnson Syndrome (SJS), drug reaction with eosinophilia and systemic symptoms (DRESS), acute generalized exanthematous pustulosis (AGEP) (see WARNINGS), anaphylaxis, angioedema, hypotension, flushing, nasal congestion, and dryness of mouth (or vagina or vulva).

RENAL: Dysuria, cystitis, polyuria, incontinence, a sense of pelvic pressure, and darkened urine.

HEPATIC: Cases of severe irreversible hepatotoxicity/acute liver failure, including cases with fatal outcomes with very rapid onset after initiation of systemic use of metronidazole, have been reported in patients with Cockayne Syndrome (latency from drug start to signs of liver failure as short as 2 days) (see CONTRAINDICATIONS).

LOCAL REACTIONS: Thrombophlebitis after intravenous infusion. This reaction can be minimized or avoided by avoiding prolonged use of indwelling intravenous catheters.

OTHER ADVERSE REACTIONS: Fever, hiccup, proliferation of Candida in the vagina, dyspareunia, decrease of libido, proctitis, and fleeting joint pains sometimes resembling “serum sickness”. If patients receiving metronidazole drink alcoholic beverages, they may experience abdominal distress, nausea, vomiting, flushing, or headache. A modification of the taste of alcoholic beverages has also been reported.

Patients with Crohn’s disease are known to have an increased incidence of gastrointestinal and certain extraintestinal cancers. There have been some reports in the medical literature of breast and colon cancer in Crohn’s disease patients who have been treated with metronidazole at high doses for extended periods of time. A cause and effect relationship has not been established. Crohn’s disease is not an approved indication for Metronidazole Injection USP.

Darkened Urine:

Instances of darkened urine have also been reported, and this manifestation has been the subject of a special investigation. Although the pigment which is probably responsible for this phenomenon has not been positively identified, it is almost certainly a metabolite of metronidazole and seems to have no clinical significance.

OVERDOSAGE

The use of dosages of metronidazole higher than those recommended has been reported. These include the use of 27 mg/kg three times a day for 20 days, and the use of 75 mg/kg as a single loading dose followed by 7.5 mg/kg maintenance doses. No adverse reactions were reported in either of the two cases.

Single oral doses of metronidazole, up to 15 g, have been reported in suicide attempts and accidental overdoses. Symptoms reported include nausea, vomiting, and ataxia.

Oral metronidazole has been studied as a radiation sensitizer in the treatment of malignant tumors. Neurotoxic effects, including seizures and peripheral neuropathy, have been reported after 5 to 7 days of doses of 6 to 10.4 g every other day.

TREATMENT:

There is no specific antidote for overdose; therefore, management of the patient should consist of symptomatic and supportive therapy.

DOSAGE AND ADMINISTRATION

RECOMMENDED DOSAGE FOR THE TREATMENT OF ANAEROBIC BACTERIAL INFECTIONS

The recommended dosage schedule for adults for the treatment of anaerobic infections is presented in Table 1:

Table 1: Recommended Dosage Schedule for the Treatment of Anaerobic Bacterial Infections in Adults

Loading Dose | 15 mg/kg infused over one hour (approximately 1 g for a 70-kg adult).
Maintenance Dose | 7.5 mg/kg infused over one hour every six hours (approximately 500 mg for a 70-kg adult). The first maintenance dose should be instituted six hours following the initiation of the loading dose.

Parenteral therapy may be changed to oral metronidazole therapy when conditions warrant, based upon the severity of the disease and the response of the patient to treatment with Metronidazole Injection. The usual adult oral dosage is 7.5 mg/kg every six hours.

A maximum of 4 grams should not be exceeded during a 24-hour period.

The usual duration of therapy is 7 to 10 days; however, infections of the bone and joint, lower respiratory tract, and endocardium may require longer treatment.

Recommended Dosage for the Treatment of Intra-Abdominal Infections in Pediatric Patients Less than 4 Months of Age:

The recommended dosage schedule for pediatric patients less than 4 months of age for the treatment of intra-abdominal infections is described in Table 2 below.

These dosage schedules achieve drug exposures in pediatric patients similar to adults treated with Metronidazole Injection for this indication.

Table 2: Recommended Dosage Schedule for the Treatment of Intra-Abdominal Infections in Pediatric Patients Less than 4 months of Age

Post-menstrual age (Completed weeks) | Loading Dose (mg/kg) | Maintenance Dose* (mg/kg) | Dosing interval (hours)
23 - < 34 | 15 | 7.5 | 12
34 – 40 | 15 | 7.5 | 8
>40 – 48 | 15 | 7.5 | 6

*The first maintenance dose is given 24 hours after the start of the loading dose.

Patients with severe hepatic disease metabolize metronidazole slowly, with resultant accumulation of metronidazole and its metabolites in the plasma. Accordingly, for such patients, doses below those usually recommended should be administered cautiously. Close monitoring of plasma metronidazole levels and toxicity is recommended.^1

In patients receiving Metronidazole Injection in whom gastric secretions are continuously removed by nasogastric aspiration, sufficient metronidazole may be removed in the aspirate to cause a reduction in serum levels.

The dose of Metronidazole Injection should not be specifically reduced in anuric patients since accumulated metabolites may be rapidly removed by dialysis.

Dosage Considerations in Geriatric Patients

In elderly patients the pharmacokinetics of metronidazole may be altered and, therefore, monitoring of serum levels may be necessary to adjust the Metronidazole Injection dosage accordingly.

RECOMMENDED PROPHYLAXIS DOSAGE

For surgical prophylactic use, to prevent postoperative infection in contaminated or potentially contaminated colorectal surgery, the recommended dosage schedule for adults is:

1. 15 mg/kg infused over 30 to 60 minutes and completed approximately one hour before surgery, followed by:
2. 7.5 mg/kg infused over 30 to 60 minutes at 6 and 12 hours after the initial dose.

It is important that (1) administration of the initial preoperative dose be completed approximately one hour before surgery so that adequate drug levels are present in the serum and tissues at the time of initial incision, and (2) Metronidazole Injection be administered, if necessary, at 6-hour intervals to maintain effective drug levels. Prophylactic use of Metronidazole Injection should be limited to the day of surgery only, following the above guidelines.

IMPORTANT PREPARATION AND ADMINISTRATION INSTRUCTIONS

Caution: Metronidazole Injection - is to be administered by slow intravenous drip infusion only, either as a continuous or intermittent infusion. IV admixtures containing metronidazole and other drugs should be avoided. Additives should not be introduced into this solution. If used with a primary intravenous fluid system, the primary solution should be discontinued during metronidazole infusion. DO NOT USE EQUIPMENT CONTAINING ALUMINUM (E.G., NEEDLES, CANNULAE) THAT WOULD COME IN CONTACT WITH THE DRUG SOLUTION.

Metronidazole Injection USP is a ready-to-use isotonic solution. NO DILUTION OR BUFFERING IS REQUIRED. Do not refrigerate. Each container of Metronidazole Injection contains 13.5 mEq of sodium.

Parenteral drug products should be inspected visually for particulate matter and discoloration prior to administration, whenever solution and container permit. Do not use if cloudy or precipitated or if the seals are not intact.

Use sterile equipment. It is recommended that the intravenous administration apparatus be replaced at least once every 24 hours.

HOW SUPPLIED

Metronidazole Injection USP, sterile, is supplied in 100 mL fill PAB® containers, each containing an isotonic, buffered solution of 500 mg metronidazole; packaged 24 per case. Metronidazole injection is sterile premixed solution intended for single use only.

NDC | REF | Fill Volume
Metronidazole Injection USP 0264-5535-32 | D5353-5224 | 100 mL

STORAGE AND HANDLING

Exposure of pharmaceutical products to heat should be minimized. Avoid excessive heat. Protect from freezing. It is recommended that the product be stored at room temperature (25°C); however, brief exposure up to 40°C does not adversely affect the product.

Protect from light until use.

REFERENCES

1. Ralph ED, Kirby WMM: Bioassay of Metronidazole With Either Anaerobic or Aerobic Incubation, J. Infect. Dis. 132:587-591 (Nov.) 1975, or Gulaid, et al.: Determination of Metronidazole and its Major Metabolites in Biological Fluids by High Pressure Liquid Chromatography, Br. J. Clin. Pharmacol. 6:430-432, 1978.

Revised: March 2025

PAB is a registered trademark of B. Braun Medical Inc.

ATCC is a registered trademark of the American Type Culture Collection.

Directions for Use of PAB® Container

CAUTION: ADDING ADDITIVES INTO THE PAB CONTAINER IS PROHIBITED. DO NOT ADD SUPPLEMENTARY MEDICATIONS.

For intravenous infusion only.

Store the individual container in the storage carton until ready to use.

Aseptic technique is required.

Before use, perform the following checks:
Read the label. Ensure solution is the one ordered and is within the expiration date.
Inspect the solution in good light for cloudiness, haze or particulate matter; check the container for leakage or damage. Any container which is suspect should not be used.
Use only if solution is clear and container and seals are intact.
Single dose plastic container.

Discard unused portion.
Consult Package Insert for complete product information.

WARNING: DO NOT USE PLASTIC CONTAINER IN SERIES CONNECTION.

1. Identify Set Port (See Figure A).
2. Caution – Adding additives into the Metronidazole Injection USP solution bag is prohibited. If used with a primary intravenous fluid system, the primary solution should be discontinued during metronidazole infusion. Do not use equipment containing aluminum (e.g., needles, cannulae, etc.) that may contact the drug solution.
3. To Attach Administration Set
  To aseptically remove the set port closure: hold container below the set port and grasp the foil tab between the thumb and forefinger then pull the tab in two steps as shown in Figure B Steps 1 and 2.
4. Push spike through the diaphragm of the port (See Figure C). Hang container using hole on the lower flap. Prime set in accordance with the Directions for Use provided with the set in use.

PAB® containers can be safely transported in a standard 6-inch carrier through a pneumatic tube system that is well maintained and running properly.

B. Braun Medical Inc.
Bethlehem, PA 18018-3524 USA
1-800-227-2862
Prepared in USA. API from Italy.

Y36-003-089 LD-438-12

PRINCIPAL DISPLAY PANEL - 100 mL fill Bag

Metronidazole Injection USP

METRONIDAZOLE
500 mg/ 100 mL (5 mg/mL)

NDC 0264-5535-32
100 mL fill

PAB® Container

For Intravenous Infusion Only.

CAUTION: ADDING ADDITIVES INTO THE PAB CONTAINER IS
PROHIBITED. DO NOT ADD SUPPLEMENTARY MEDICATIONS.

Single dose plastic container. Discard unused portion.
Protect from light until use.

Each 100 mL contains: Metronidazole USP 500 mg; Sodium
Chloride USP 740 mg; Dibasic Sodium Phosphate•7H2O USP
112 mg; Citric Acid Anhydrous USP 40 mg; Water for Injection USP, qs

pH: 5.8 (4.5-7.0) Calc. Osmolarity: 297 mOsmol/liter
Sodium content: 13.5 mEq/container

Sterile, nonpyrogenic. Use only if solution is clear and container and
seals are intact. For intravenous use only.

Recommended Storage: Room temperature (25°C). Avoid
excessive heat. Protect from freezing. See Package Insert.

Not made with natural rubber latex, PVC or DEHP.

Rx only

PAB is a registered trademark of B. Braun Medical Inc.

REF D5353-5224 HK 41283
B. Braun Medical Inc.
Bethlehem, PA 18018-3524 USA
1-800-227-2862
Prepared in USA. API from Italy.

Y94-003-379 LD-491-4

LOT

EXP

PRINCIPAL DISPLAY PANEL - 100 mL fill Container Carton

Metronidazole Injection USP

METRONIDAZOLE
500 mg/ 100 mL (5 mg/mL)

Four 100 mL fill PAB® Containers

NDC 0264-5535-32

For Intravenous Infusion Only.

CAUTION: ADDING ADDITIVES INTO THE PAB CONTAINER IS
PROHIBITED. DO NOT ADD SUPPLEMENTARY MEDICATIONS.

Single dose plastic container. Discard unused portion.
Protect from light until use.

Each 100 mL contains: Metronidazole USP 500 mg; Sodium Chloride
USP 740 mg; Dibasic Sodium Phosphate•7H2O USP 112 mg;
Citric Acid Anhydrous USP 40 mg; Water for Injection USP, qs

pH: 5.8 (4.5-7.0) Calc. Osmolarity: 297 mOsmol/liter
Sodium content: 13.5 mEq/container

Sterile, nonpyrogenic. Use only if solution is clear and container
and seals are intact. For intravenous use only.

Recommended Storage: Room temperature (25°C). Avoid
excessive heat. Protect from freezing. See Package Insert.

Not made with natural rubber latex, PVC or DEHP.

Rx only

PAB is a registered trademark of B. Braun Medical Inc.

REF D5353-5224 HK 41283

B. Braun Medical Inc.
Bethlehem, PA 18018-3524 USA
1-800-227-2862
Prepared in USA. API from Italy.

X12-002-495 LD-492-4

LOT

EXP